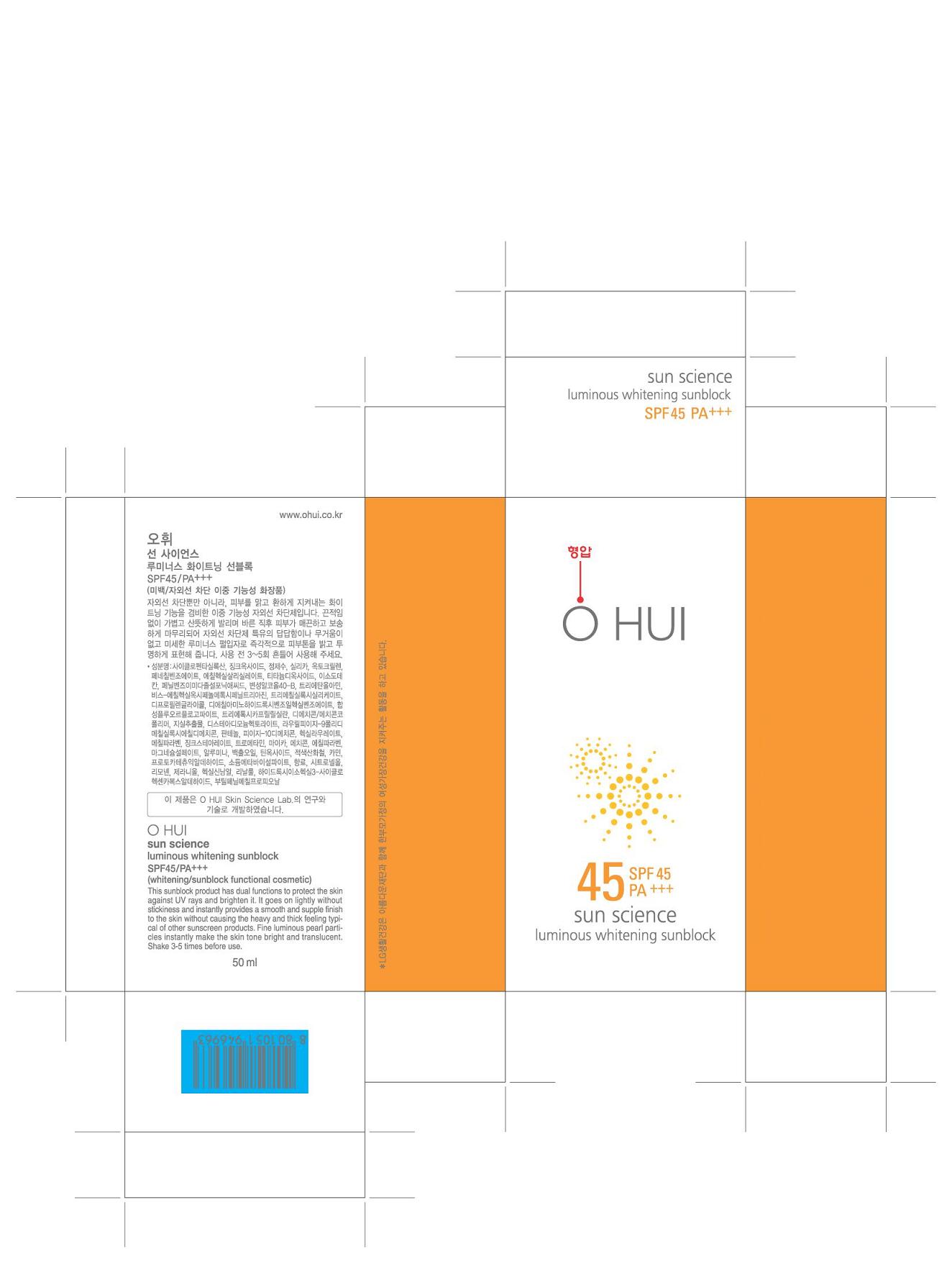 DRUG LABEL: OHUI SUNSCIENCE LUMINOUS WHITENING SUNBLOCK
NDC: 53208-518 | Form: CREAM
Manufacturer: LG Household and Healthcare, Inc.
Category: otc | Type: HUMAN OTC DRUG LABEL
Date: 20110407

ACTIVE INGREDIENTS: ENSULIZOLE 3.9 mL/100 mL; OCTISALATE 4.7 mL/100 mL; BEMOTRIZINOL 1.5 mL/100 mL; OCTOCRYLENE 5 mL/100 mL; DIETHYLAMINO HYDROXYBENZOYL HEXYL BENZOATE 1 mL/100 mL; ZINC OXIDE 12.3 mL/100 mL; TITANIUM DIOXIDE 3.67 mL/100 mL; ATRACTYLODES JAPONICA ROOT OIL 0.525 mL/100 mL
INACTIVE INGREDIENTS: WATER; ALCOHOL; TROLAMINE; TROMETHAMINE; PANTHENOL; DIPROPYLENE GLYCOL; PONCIRUS TRIFOLIATA FRUIT; METHYLPARABEN; ETHYLPARABEN; MAGNESIUM SULFATE, UNSPECIFIED; CYCLOMETHICONE 5; HECTORITE; ZINC STEARATE; PHENETHYL BENZOATE; SILICON DIOXIDE; ISODODECANE

Drug Fact

ACTIVE INGREDIENT

ENSULIZOLE 3.9%
OCTISALATE 4.7%
BEMOTRIZINOL 1.5%
OCTOCRYLENE 5%
DIETHYLAMINO HYDROXYBENZOYL HEXYL BENZOATE 1%
ZINC OXIDE 12.3%
TITANIUM DIOXIDE 3.67%
ATRACTYLODES JAPONICA ROOT OIL 0.0525%

WARNINGS AND PRECAUTIONS

For external use only.

Keep out of reach of children. Is swallowed, get medical help or contact a Poison Control Center right away.

WHEN USING

Keep out of eyes. Rinse with water to remove.